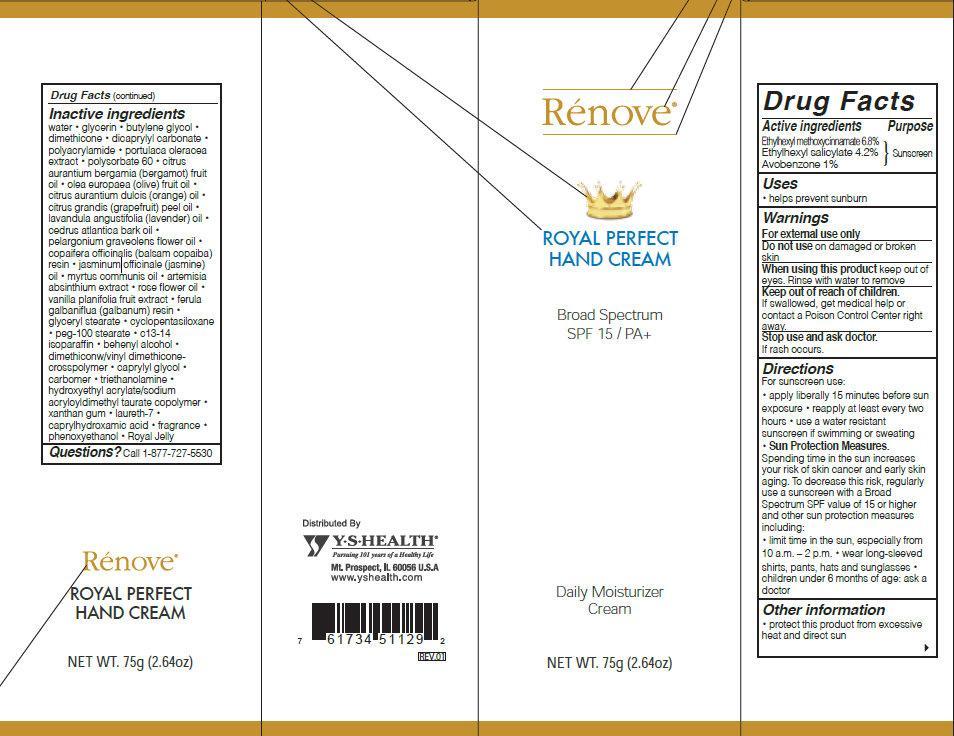 DRUG LABEL: Renove ROYAL PERFECT HAND Broad Spectrum SPF 15
NDC: 60782-001 | Form: CREAM
Manufacturer: YS Health Corp.
Category: otc | Type: HUMAN OTC DRUG LABEL
Date: 20131205

ACTIVE INGREDIENTS: OCTINOXATE 68 mg/1 g; OCTISALATE 42 mg/1 g; AVOBENZONE 10 mg/1 g
INACTIVE INGREDIENTS: WATER; GLYCERIN; BUTYLENE GLYCOL; DIMETHICONE; DICAPRYLYL CARBONATE; POLYSORBATE 60; BERGAMOT OIL; OLIVE OIL; ORANGE OIL; CITRUS MAXIMA FRUIT RIND OIL; LAVENDER OIL; CEDRUS ATLANTICA BARK OIL; PELARGONIUM GRAVEOLENS FLOWER OIL; COPAIFERA OFFICINALIS RESIN; JASMINUM OFFICINALE FLOWER; MYRTLE LEAF OIL; WORMWOOD; ROSA RUGOSA FLOWER BUD; VANILLA; GALBANUM OIL; GLYCERYL MONOSTEARATE; CYCLOMETHICONE 5; PEG-100 STEARATE; C13-14 ISOPARAFFIN; DOCOSANOL; CAPRYLYL GLYCOL; TROLAMINE; XANTHAN GUM; LAURETH-7; CAPRYLHYDROXAMIC ACID; PHENOXYETHANOL; ROYAL JELLY

Renove ROYAL PERFECT HAND CREAM Broad Spectrum SPF 15

Active ingredients

Ethylhexyl methoxycinnamate 6.8%
Ethylhexyl salicylate 4.2%
Avobenzone 1%

Purpose

Sunscreen

Uses

- helps prevent sunburn

Warnings

For external use only

Do not use

on damaged or broken skin

When using this product

keep out of eyes. Rinse with water to remove

Keep out of reach of children.

If swallowed, get medical help or contact a Poison Control Center right away.

Stop use and ask doctor.

If rash occurs.

Directions

For sunscreen use:

- Apply liberally 15 minutes before sun exposure
- reapply at least every two hours
- use a water resistant sunscreen if swimming or sweating
- Sun Protection Measures. Spending time in the sun increases your risk of skin cancer and early skin aging. To decrease this risk, regularly use a sunscreen with a Broad Spectrum SPF value of 15 or higher and other sun protection measures including:
-
  - Limit time in the sun, especially from 10 a.m. - 2 p.m.
  - Wear long-sleeved shirts, pants, hats and sunglasses
- Children under 6 months of age: Ask a doctor

Other information

- protect this product from excessive heat and direct sun

Inactive ingredients

water・glycerin ・butylene glycol・dimethicone・dicaprylyl carbonate・polyacrylamide・portulaca oleracea extract・polysorbate 60・citrus aurantium bergamia (bergamot) fruit oil・olea europaea (olive) fruit oil・citrus aurantium dulcis (orange) oil・citrus grandis (grapefruit) peel oil・lavandula angustifolia (lavender) oil・cedrus atlantica bark oil・pelargonium graveolens flower oil・copaifera officinalis (balsam copaiba) resin・jasminum officinale (jasmine) oil・myrtus communis oil・Artemisia absinthium extract・ rose flower oil・vanilla planifolia fruit extract・ferula galbaniflua galbanum) resin・glyceryl stearate・ cyclopentasiloxane・peg-100 stearate・c13-14 isoparaffin・behenyl alcohol・dimethiconw/vinyl dimethiconecrosspolymer・caprylyl glycol・carbomer・triethanolamine・hydroxyethyl acrylate/sodium acryloyldimethyl taurate copolymer・xanthan gum・laureth-7・caprylhydroxamic acid・fragrance ・phenoxyethanol・Royal Jelly

Questions?

Call 1-877-727-5530